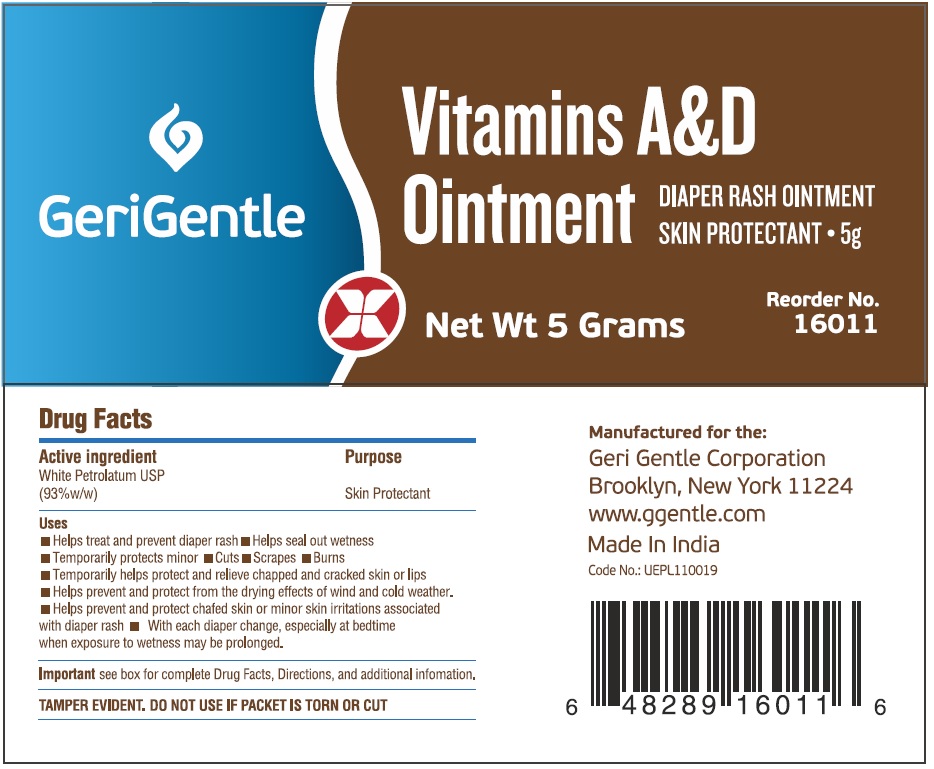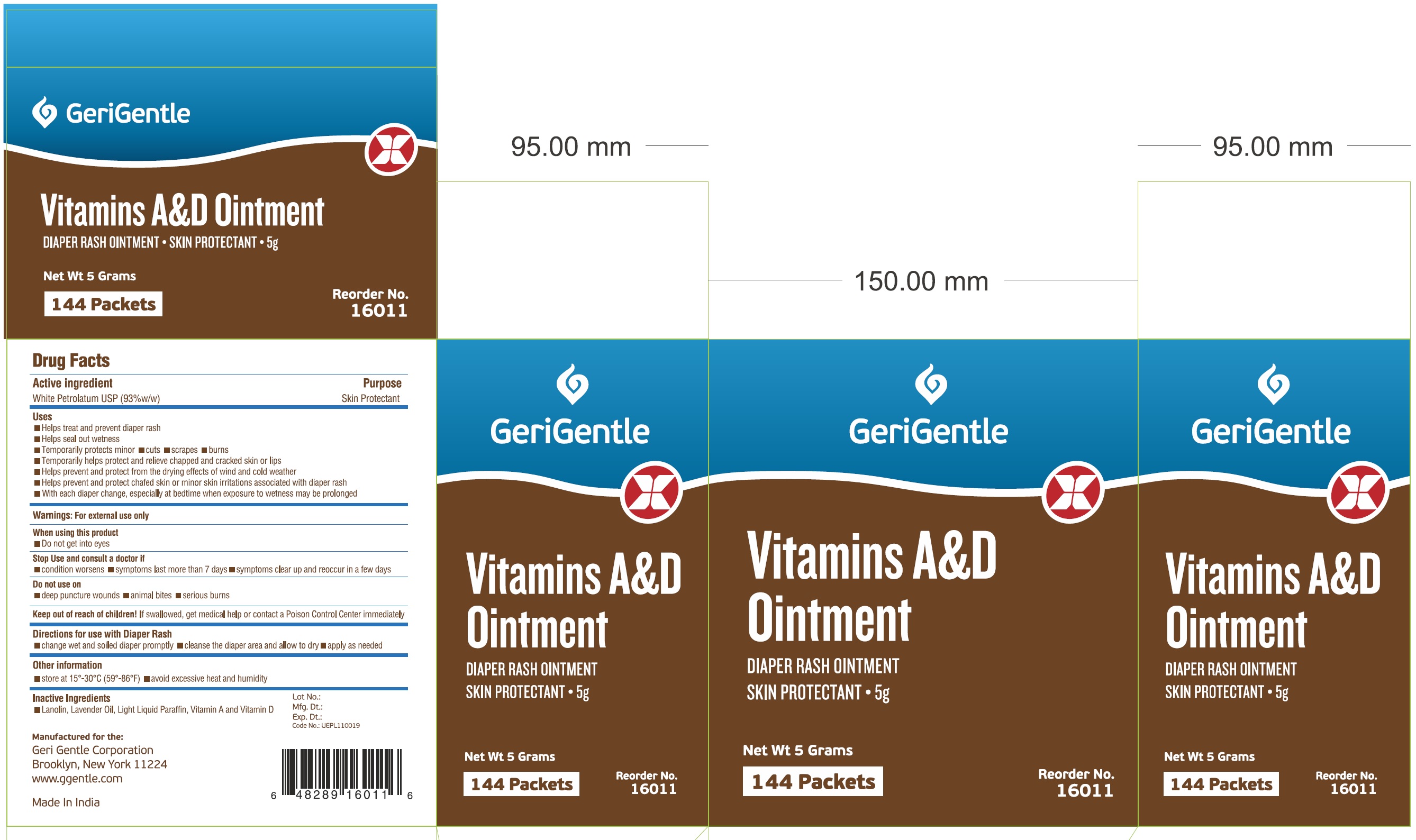 DRUG LABEL: Vitamins A and D
NDC: 69771-009 | Form: OINTMENT
Manufacturer: Geri-Gentle Corporation
Category: otc | Type: HUMAN OTC DRUG LABEL
Date: 20211110

ACTIVE INGREDIENTS: PETROLATUM 930 mg/1 g
INACTIVE INGREDIENTS: LANOLIN; LAVENDER OIL; PARAFFIN; VITAMIN A; VITAMIN D

Vitamins A&D Ointment

Active ingredient

White Petrolatum USP (93%w/w)

Purpose

Skin Protectant

Uses

- Helps treat and prevent diaper rash
- Helps seal out wetness
- Temporarily protects minor
- cuts
- scrapes
- burns
- Temporarily helps protect and relieve chapped and cracked skin or lips
- Helps prevent and protect from the drying effects of wind and cold weather
- Helps prevent and protect chafed skin or minor skin irritations associated with diaper rash
- With each diaper change, especially at bedtime when exposure to wetness may be prolonged

Warnings:

For external use only

When using this product

- Do not get into eyes

Stop Use and consult a doctor if

- condition worsens
- symptoms last more than 7 days
- symptoms clear up and reoccur in a few days

Do not use on

- deep punture wounds
- animal bites
- serious burns

Keep out of reach of children.

If swallowed, get medical help or contact a Poison Control Center immediately

Directions for use with Diaper Rash

- change wet and soiled diaper promptly
- cleanse the diaper area and allow to dry
- apply as needed

Other information

- store at 15°-30°C (59°-86°F)
- avoid excessive heat and humidity

Inactive Ingredients

Lanolin, Lavender Oil, Light Liquid Paraffin, Vitamin A and Vitamin D